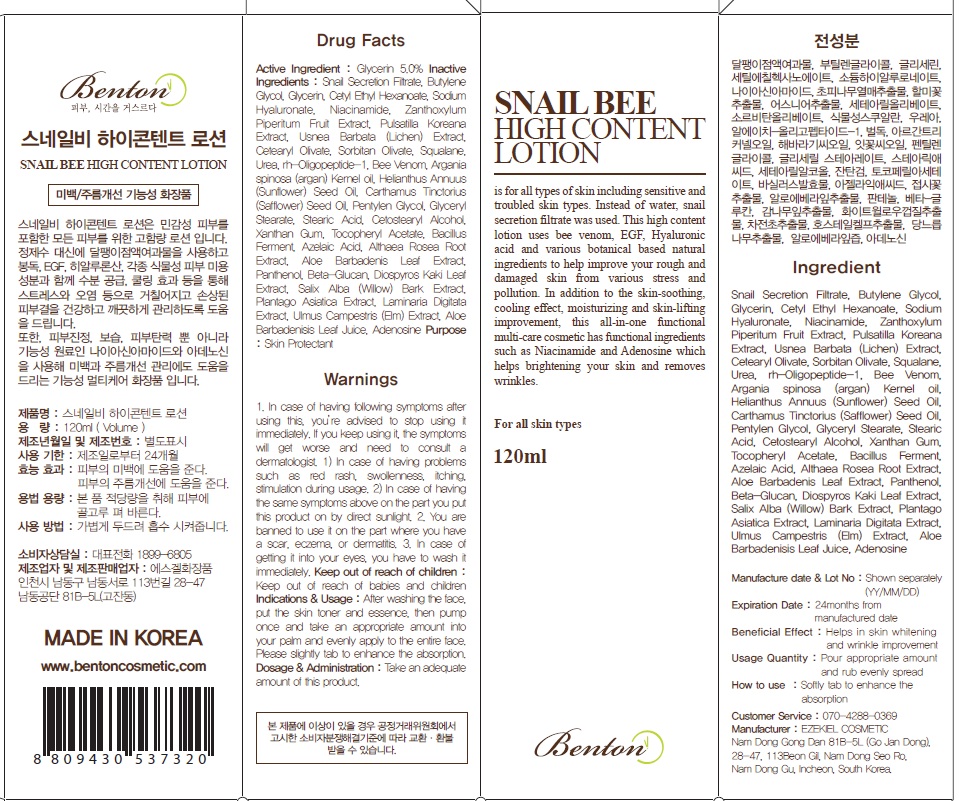 DRUG LABEL: SNAIL BEE HIGH CONTENT
NDC: 69998-080 | Form: LOTION
Manufacturer: BENTON KOREA
Category: otc | Type: HUMAN OTC DRUG LABEL
Date: 20160624

ACTIVE INGREDIENTS: Glycerin 6.0 g/120 mL
INACTIVE INGREDIENTS: Butylene Glycol; Niacinamide

ACTIVE INGREDIENT

Active Ingredient: Glycerin 5.0%

INACTIVE INGREDIENT

Inactive Ingredients: Snail Secretion Filtrate, Butylene Glycol, Cetyl Ethyl Hexanoate, Sodium Hyaluronate, Niacinamide, Zanthoxylum Piperitum Fruit Extract, Pulsatilla Koreana Extract, Usnea Barbata (Lichen) Extract, Cetearyl Olivate, Sorbitan Olivate, Phytosqualane, Urea, Argania spinosa (argan)Kernel oil, Helianthus Annuus (Sunflower) Seed Oil, Carthamus Tinctorius (Safflower) Seed Oil, Pentylen Glycol, rh-Oligopeptide-1, Glyceryl Stearate, Stearic Acid, Cetostearyl Alcohol, Xanthan Gum, Tocopheryl Acetate, Bacillus Ferment, Azelaic Acid, Althaea Rosea Root Extract, Aloe Barbadenis Leaf Extract, Panthenol, Beta-Glucan, Salix Nigra (Willow) Bark Exrtact, Plantago Asiatica Exrtact, Laminaria Digitata Exrtact, Ulmus Campestris (Elm) Extract, Aloe Barbadenisis Leaf Juice, Adenosine, Bee Venom

PURPOSE

Purpose: Skin Protectant

WARNINGS

Warnings: 1. In case of having following symptoms after using this, you’re advised to stop using it immediately. If you keep using it, the symptoms will get worse and need to consult a dermatologist. 1) In case of having problems such as red rash, swollenness, itching, stimulation during usage. 2) In case of having the same symptoms above on the part you put this product on by direct sunlight. 2. You are banned to use it on the part where you have a scar, eczema, or dermatitis. 3. In case of getting it into your eyes, you have to wash it immediately.

Keep out of reach of children: Keep out of reach of babies and children

INDICATIONS & USAGE

Indications & Usage: After washing the face, put the skin toner and essence, then pump once and take an appropriate amount into your palm and evenly apply to the entire face. Please slightly tap to enhance the absorption.

DOSAGE & ADMINISTRATION

Dosage & Administration: Take an adequate amount of this product.